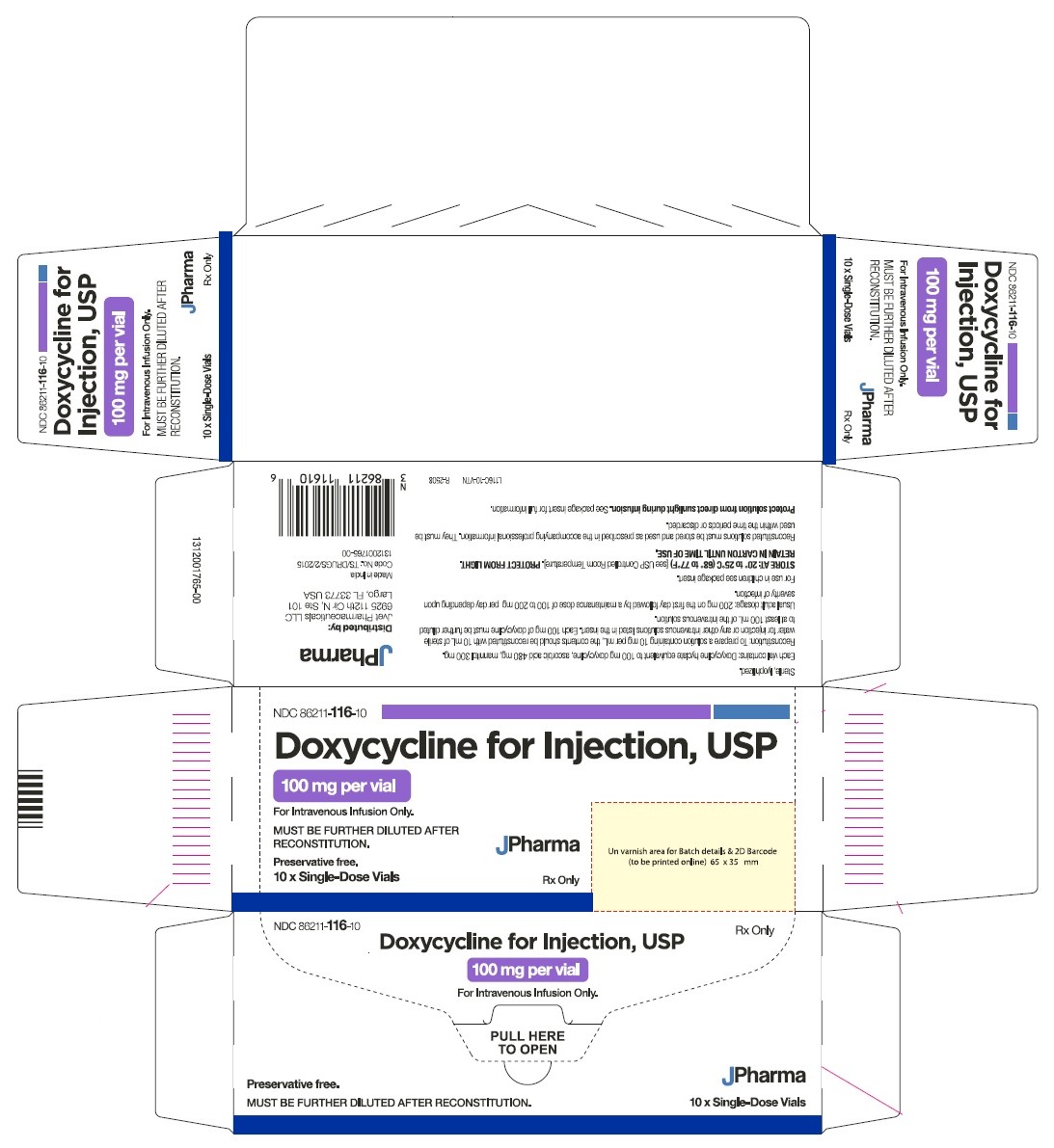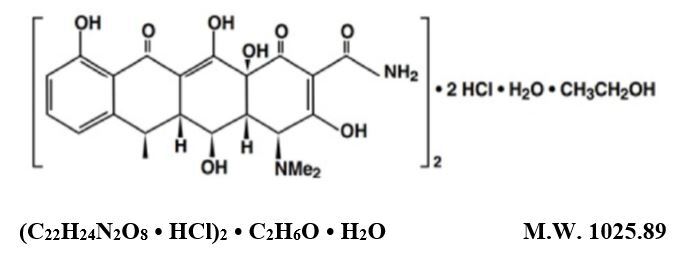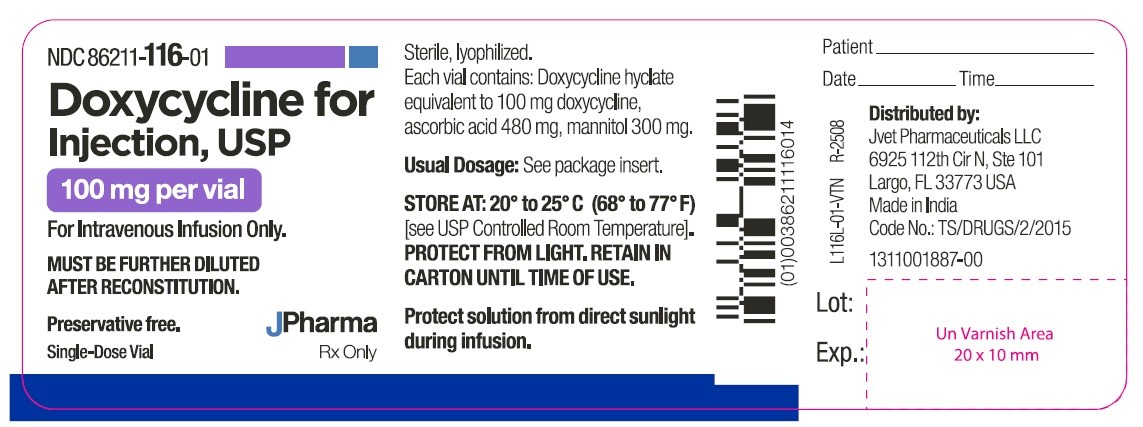 DRUG LABEL: DOXYCYCLINE
NDC: 86211-116 | Form: INJECTION, POWDER, LYOPHILIZED, FOR SOLUTION
Manufacturer: JVET PHARMACEUTICALS LLC
Category: prescription | Type: HUMAN PRESCRIPTION DRUG LABEL
Date: 20260127

ACTIVE INGREDIENTS: DOXYCYCLINE HYCLATE 100 mg/10 mL
INACTIVE INGREDIENTS: ASCORBIC ACID 480 mg/10 mL; MANNITOL 300 mg/10 mL

Doxycycline for Injection, USP
FOR INTRAVENOUS INFUSION ONLY
To reduce the development of drug –resistant bacteria and maintain the effectiveness of Doxycycline for Injection, USP and other antibacterial drugs, Doxycycline for Injection, USP should be used only to treat or prevent infections that are proven or strongly suspected to be caused by bacteria.

DESCRIPTION

Doxycycline for Injection, USP is a sterile, lyophilized powder prepared from a solution of doxycycline hyclate, ascorbic acid and mannitol in Water for Injection. Doxycycline hyclate is a broad spectrum antibiotic derived from oxytetracycline. It is meant for INTRAVENOUS use only after reconstitution. Doxycycline hyclate is a yellowish crystalline powder which is chemically designated 4-(Dimethylamino)-1,4,4a,5,5a,6,11,12a-octahydro-3,5,10,12,12a-pentahydroxy-6-methyl-1,11-demonohydrochloride, compound with ethyl alcohol (2:1), monohydrate. It has the following structural formula:

Doxycycline hyclate is soluble in water and chars at 201°C without melting. The base doxycycline has a high degree of lipid solubility and a low affinity for calcium binding. It is highly stable in normal human serum.

Each 100 mg vial contains: Doxycycline hyclate equivalent to 100 mg doxycycline; ascorbic acid 480 mg; mannitol 300 mg. pH of the reconstituted solution (10 mg/mL) is between 1.8 and 3.3.

CLINICAL PHARMACOLOGY

Tetracyclines are readily absorbed and are bound to plasma proteins in varying degree. They are concentrated by the liver in the bile, and excreted in the urine and feces at high concentrations and in a biologically active form.

Following a single 100 mg dose administered in a concentration of 0.4 mg/mL in a one-hour infusion, normal adult volunteers averaged a peak of 2.5 mcg/mL, while 200 mg of a concentration of 0.4 mg/mL administered over two hours averaged a peak of 3.6 mcg/mL.

Excretion of doxycycline by the kidney is about 40 percent/72 hours in individuals with normal function (creatinine clearance about 75 mL/min). This percentage of excretion may fall as low as 1 to 5 percent/72 hours in individuals with severe renal insufficiency (creatinine clearance below 10 mL/min). Studies have shown no significant difference in serum half-life of doxycycline (range 18 to 22 hours) in individuals with normal and severely impaired renal function.

Hemodialysis does not alter this serum half-life of doxycycline.

Population pharmacokinetic analysis of sparse concentration-time data of doxycycline following standard of care intravenous and oral dosing in 44 pediatric patients (2-18 years of age) showed that allometrically-scaled clearance (CL) of doxycycline in pediatric patients ≥2 to ≤8 years of age (median [range] 3.58 [2.27-10.82] L/h/70 kg, N=11) did not differ significantly from pediatric patients ˃8 to 18 years of age (3.27 [1.11-8.12] L/h/70 kg, N=33). For pediatric patients weighing ≤45 kg, body weight normalized doxycycline CL in those ≥2 to ≤8 years of age (median [range] 0.071 [0.041-0.202] L/kg/h, N=10) did not differ significantly from those ˃8 to 18 years of age (0.081 [0.035-0.126] L/kg/h, N=8) In pediatric patients weighing ˃45 kg, no clinically significant differences in body weight normalized doxycycline CL were observed between those ≥2 to ≤8 years of age (0.050 L/kg/h, N=1) and those ˃8 to 18 years of age (0.044 [0.014-0.121] L/kg/h, N=25). No clinically significant difference in CL between oral and IV dosing was observed in the small cohort of pediatric patients who received the oral (N=19) or IV (N=21) formulation alone.

Microbiology

Mechanism of Action

Doxycycline inhibits bacterial protein synthesis by binding to the 30S ribosomal subunit. Doxycycline has bacteriostatic activity against a broad range of Gram-positive and Gram-negative bacteria.

Resistance

Cross resistance with other tetracyclines is common.

Antimicrobial Activity

Doxycycline has been shown to be active against most isolates of the following microorganisms, both in vitro and in clinical infections (see INDICATIONS AND USAGE).

Gram-Negative Bacteria

Acinetobacter species

Bartonella bacilliformis

Brucella species

Enterobacter aerogenes

Escherichia coli

Francisella tularensis

Haemophilus ducreyi

Haemophilus influenzae

Klebsiella granulomatis

Klebsiella species

Neisseria gonorrhoeae

Shigella species

Vibrio cholerae

Campylobacter fetus

Yersinia pestis

Gram-Positive Bacteria

Bacillus anthracis

Listeria monocytogenes

Streptococcus pneumoniae

Anaerobic Bacteria

Clostridium species

Fusobacterium fusiforme

Propionibacterium acnes

Other Bacteria

Nocardiae and other aerobic Actinomyces species

Borrelia recurrentis

Chlamydophila psittaci

Chlamydia trachomatis

Mycoplasma pneumoniae

Rickettsiae

Treponema pallidum

Treponema pallidum subspecies pertenue

Ureaplasma urealyticum

Parasites

Balantidium coli

Entamoeba species

Plasmodium falciparum*

*Doxycycline has been found to be active against the asexual erythrocytic forms of Plasmodium falciparum but not against the gametocytes of P. falciparum. The precise mechanism of action of the drug is not known.

Susceptibility Testing

For specific information regarding susceptibility test interpretive criteria and associated test methods and quality control standards recognized by FDA for this drug, please see: https://www.fda.gov/STIC.

INDICATIONS AND USAGE

To reduce the development of drug-resistant bacteria and maintain the effectiveness of Doxycycline for Injection, USP and other antibacterial drugs, Doxycycline for Injection, USP should be used only to treat or prevent infections that are proven or strongly suspected to be caused by susceptible bacteria. When culture and susceptibility information are available, they should be considered in selecting or modifying antibacterial therapy. In the absence of such data, local epidemiology and susceptibility patterns may contribute to the empiric selection of therapy.

Doxycycline for Injection, USP is indicated in infections caused by the following microorganisms:

- Rickettsiae (Rocky Mountain spotted fever, typhus fever, and the typhus group, Q fever, rickettsial pox and tick fevers).
- Mycoplasma pneumoniae (PPLO, Eaton Agent).
- Agents of psittacosis and ornithosis.
- Agents of lymphogranuloma venereum and granuloma inguinale.
- The spirochetal agent of relapsing fever (Borrelia recurrentis).

The following gram-negative microorganisms:

- Haemophilus ducreyi (chancroid).
- Yersinia pestis and Francisella tularensis.
- Bartonella bacilliformis.•Bacteroides species.
- Vibrio cholerae and Campylobacter fetus.
- Brucella species (in conjunction with streptomycin).

Because many strains of the following groups of microorganisms have been shown to be resistant to tetracyclines, culture and susceptibility testing are recommended.

Doxycycline is indicated for treatment of infections caused by the following gram-negative microorganisms when bacteriologic testing indicates appropriate susceptibility to the drug:

- Escherichia coli.
- Enterobacter aerogenes.
- Shigella species.•Acinetobacter species.
- Haemophilus influenzae (respiratory infections).
- Klebsiella species (respiratory and urinary infections).

Doxycycline is indicated for treatment of infections caused by the following gram-positive microorganisms when bacteriologic testing indicates appropriate susceptibility to the drug:

- Streptococcus species:

Up to 44 percent of strains of Streptococcus pyogenes and 74 percent of Enterococcus faecalis have been found to be resistant to tetracycline drugs. Therefore, tetracyclines should not be used for streptococcal disease unless the organism has been demonstrated to be sensitive.

For upper respiratory infections due to group A beta-hemolytic streptococci, penicillin is the usual drug of choice, including prophylaxis of rheumatic fever.

- Streptococcus pneumoniae.
- Staphylococcus aureus, respiratory, skin and soft tissue infections. Tetracyclines are not the drugs of choice in the treatment of any type of staphylococcal infections.
- Anthrax due to Bacillus anthracis, including inhalational anthrax (post-exposure): to reduce the incidence or progression of disease following exposure to aerosolized Bacillus anthracis.

When penicillin is contraindicated, doxycycline is an alternative drug in the treatment of infections due to:

- Neisseria gonorrhoeae and N. meningitidis.
- Treponema pallidum and Treponema pallidum subspecies pertenue (syphilis and yaws).
- Listeria monocytogenes.
- Clostridium species.
- Fusobacterium fusiforme (Vincent's infection).
- Actinomyces species.

In acute intestinal amebiasis, doxycycline may be a useful adjunct to amebicides.

Doxycycline is indicated in the treatment of trachoma, although the infectious agent is not always eliminated, as judged by immunofluorescence.

CONTRAINDICATIONS

This drug is contraindicated in persons who have shown hypersensitivity to any of the tetracyclines.

WARNINGS

The use of drugs of the tetracycline class during tooth development (last half of pregnancy, infancy and childhood to the age of 8 years) may cause permanent discoloration of the teeth (yellow-gray-brown). This adverse reaction is more common during long-term use of the drugs but has been observed following repeated short-term courses. Enamel hypoplasia has also been reported. Use doxycycline in pediatric patients 8 years of age or less only when the potential benefits are expected to outweigh the risks in severe or life-threatening conditions (e.g., anthrax, Rocky Mountain spotted fever), particularly when there are no alternative therapies.

Clostridium difficile associated diarrhea (CDAD) has been reported with use of nearly all antibacterial agents, including doxycycline for injection, USP, and may range in severity from mild diarrhea to fatal colitis. Treatment with antibacterial agents alters the normal flora of the colon leading to overgrowth of C. difficile.

C. difficile produces toxins A and B which contribute to the development of CDAD. Hypertoxin producing strains of C. difficile cause increased morbidity and mortality, as these infections can be refractory to antimicrobial therapy and may require colectomy. CDAD must be considered in all patients who present with diarrhea following antibiotic use. Careful medical history is necessary since CDAD has been reported to occur over two months after the administration of antibacterial agents

If CDAD is suspected or confirmed, ongoing antibiotic use not directed against C. difficile may need to be discontinued. Appropriate fluid and electrolyte management, protein supplementation, antibiotic treatment of C. difficile, and surgical evaluation should be instituted as clinically indicated.

Severe skin reactions, such as exfoliative dermatitis, erythema multiforme, Stevens-Johnson syndrome, toxic epidermal necrolysis, and drug reaction with eosinophilia and systemic symptoms (DRESS) have been reported in patients receiving doxycycline. Fixed drug eruptions have occurred with doxycycline and have been associated with worsening severity upon subsequent administrations, including generalized bullous fixed drug eruption (see ADVERSE REACTIONS). If severe skin reactions occur, discontinue doxycycline immediately and institute appropriate therapy.

Intracranial hypertension (IH, pseudotumor cerebri) has been associated with the use of tetracyclines including doxycycline. Clinical manifestations of IH include headache, blurred vision, diplopia, and vision loss; papilledema can be found on fundoscopy. Women of childbearing age who are overweight or have a history of IH are at greater risk for developing tetracycline associated IH. Concomitant use of isotretinoin and doxycycline should be avoided because isotretinoin is also known to cause pseudotumor cerebri.

Although IH typically resolves after discontinuation of treatment, the possibility for permanent visual loss exists. If visual disturbance occurs during treatment, prompt ophthalmologic evaluation is warranted. Since intracranial pressure can remain elevated for weeks after drug cessation patients should be monitored until they stabilize.

Photosensitivity manifested by an exaggerated sunburn reaction has been observed in some individuals taking tetracyclines. Patients apt to be exposed to direct sunlight or ultraviolet light, should be advised that this reaction can occur with tetracycline drugs, and treatment should be discontinued at the first evidence of skin erythema.

The anti-anabolic action of the tetracyclines may cause an increase in BUN. Studies to date indicate that this does not occur with the use of doxycycline in patients with impaired renal function.

PRECAUTIONS

General

As with other antibacterial drugs, use of doxycycline may result in overgrowth of nonsusceptible organisms, including fungi. If superinfection occurs, doxycycline should be discontinued and appropriate therapy instituted.

Incision and drainage or other surgical procedures should be performed in conjunction with antibacterial therapy, when indicated.

Prescribing doxycycline in the absence of proven or strongly suspected bacterial infection or a prophylactic indication is unlikely to provide benefit to the patient and increases the risk of the development of drug-resistant bacteria.

All infections due to group A beta-hemolytic streptococci should be treated for at least 10 days.

Information for Patients

Patients taking doxycycline should be advised:•to avoid excessive sunlight or artificial ultraviolet light while receiving doxycycline and to discontinue therapy if phototoxicity (e.g., skin eruption, etc.) occurs. Sunscreen or sunblock should be considered. (SeeWARNINGS.)•that the use of doxycycline might increase the incidence of vaginal candidiasis. Patients should be counseled that antibacterial drugs, including doxycycline should only be used to treat bacterial infections. They do not treat viral infections (e.g., the common cold). When doxycycline is prescribed to treat a bacterial infection, patients should be told that although it is common to feel better early in the course of therapy, the medication should be taken exactly as directed. Skipping doses or not completing the full course of therapy may (1) decrease the effectiveness of the immediate treatment and (2) increase the likelihood that bacteria will develop resistance and will not be treatable by doxycycline or other antibacterial drugs in the future.
Diarrhea is a common problem caused by antibacterial drugs, which usually ends when the antibacterials are discontinued. Sometimes after starting treatment with antibacterial drugs, patients can develop watery and bloody stools (with or without stomach cramps and fever) even as late as two or more months after having taken the last dose of the antibacterial drug. If this occurs, patients should contact their physician as soon as possible.

Laboratory Tests

In venereal diseases when coexistent syphilis is suspected, a dark field examination should be done before treatment is started and the blood serology repeated monthly for at least 4 months.

In long-term therapy, periodic laboratory evaluation of organ systems, including hematopoietic, renal, and hepatic studies should be performed.

Drug Interactions

Because tetracyclines have been shown to depress plasma prothrombin activity, patients who are on anticoagulant therapy may require downward adjustment of their anticoagulant dosage.

Since bacteriostatic drugs may interfere with the bactericidal action of penicillin, it is advisable to avoid giving tetracycline in conjunction with penicillin.

Barbiturates, carbamazepine, and phenytoin decrease the half-life of doxycycline.

The concurrent use of tetracycline and Penthrane® (methoxyflurane) has been reported to result in fatal renal toxicity.

Concurrent use of tetracycline may render oral contraceptives less effective.

Usage in Pregnancy

(See WARNINGS about use during tooth development.)

Doxycycline for Injection has not been studied in pregnant patients. It should not be used in pregnant women unless, in the judgment of the physician, it is essential for the welfare of the patient.

Results of animal studies indicate that tetracycline cross the placenta, are found in fetal tissues and can have toxic effects on the developing fetus (often related to retardation of skeletal development). Evidence of embryotoxicity has also been noted in animals treated early in pregnancy.

Usage in Children

The use of Doxycycline for Injection in children under 8 years is not recommended because safe conditions for its use have not been established. Because of the effects of drugs of the tetracycline-class on tooth development and growth, use of doxycycline in pediatric patients 8 years of age or less only when the potential benefits are expected to outweigh the risks in severe or life-threatening conditions (e.g., anthrax, Rocky Mountain spotted fever), particularly when there are no alternative therapies (see WARNINGS and DOSAGE AND ADMINISTRATION).

As with other tetracyclines, doxycycline forms a stable calcium complex in any bone-forming tissue. A decrease in the fibula growth rate has been observed in prematures given oral tetracycline in doses of 25 mg/kg every 6 hours. This reaction was shown to be reversible when the drug was discontinued.

Tetracyclines are present in the milk of lactating women who are taking a drug in this class.

ADVERSE REACTIONS

Gastrointestinal
Anorexia, nausea, vomiting, diarrhea, glossitis, dysphagia, enterocolitis and inflammatory lesions (with monilial overgrowth) in the anogenital region, and pancreatitis. Hepatotoxicity has been reported rarely. These reactions have been caused by both the oral and parenteral administration of tetracyclines. Superficial discoloration of the adult permanent dentition, reversible upon drug discontinuation and professional dental cleaning has been reported. Permanent tooth discoloration and enamel hypoplasia may occur with drugs of the tetracycline class when used during tooth development (see WARNINGS).

Skin
Maculopapular and erythematous rashes and fixed drug eruption have been reported. Exfoliative dermatitis has been reported but is uncommon. Photosensitivity is discussed above (see WARNINGS).

Renal Toxicity
Rise in BUN has been reported and is apparently dose related (see WARNINGS).

Immune
Hypersensitivity reactions including urticaria, angioneurotic edema, anaphylaxis, anaphylactoid purpura, pericarditis and exacerbation of systemic lupus erythematosus, drug reaction with eosinophilia and systemic symptoms (DRESS).

Other
Bulging fontanels in infants and intracranial hypertension in adults (see WARNINGS).

Blood
Hemolytic anemia, thrombocytopenia, neutropenia and eosinophilia have been reported.

Psychiatric

Depression, anxiety, suicidal ideation, insomnia, abnormal dreams, hallucination.

When given over prolonged periods, tetracyclines have been reported to produce brown-black microscopic discoloration of thyroid glands. No abnormalities of thyroid function studies are known to occur.

To report SUSPECTED ADVERSE REACTIONS, contact Jvet Pharmaceuticals at 1-727-292-1166 or FDA at 1-800-FDA-1088 or www.fda.gov/medwatch.

DOSAGE AND ADMINISTRATION

NOTE: Rapid administration is to be avoided. Parenteral therapy is indicated only when oral therapy is not indicated. Oral therapy should be instituted as soon as possible. If intravenous therapy is given over prolonged periods of time, thrombophlebitis may result.

The usual dosage and frequency of administration of Doxycycline for Injection (100 to 200 mg/day) differs from that of the other tetracyclines (1 to 2 g/day). Exceeding the recommended dosage may result in an increased incidence of side effects.

Studies to date have indicated that doxycycline hyclate at the usual recommended doses does not lead to excessive accumulation of the antibiotic in patients with renal impairment.

Adults

The usual dosage of doxycycline for injection is 200 mg on the first day of treatment administered in one or two infusions. Subsequent daily dosage is 100 to 200 mg depending upon the severity of infection, with 200 mg administered in one or two infusions.

In the treatment of primary and secondary syphilis, the recommended dosage is 300 mg daily for at least 10 days.

In the treatment of inhalational anthrax (post-exposure) the recommended dose is 100 mg of doxycycline, twice a day. Parenteral therapy is only indicated when oral therapy is not indicated and should not be continued over a prolonged period of time. Oral therapy should be instituted as soon as possible. Therapy must continue for a total of 60 days.

Pediatric Patients

For all pediatric patients weighing less than 45 kg with severe or life-threatening infections (e.g., anthrax, Rocky Mountain spotted fever), the recommended dosage is 2.2 mg/kg of body weight administered every 12 hours. Children weighing 45 kg or more should receive the adult dose (see WARNINGS and PRECAUTIONS).

For pediatric patients with less severe disease (greater than 8 years of age and weighing less than 45 kg), the recommended dosage schedule is 4.4 mg/kg of body weight divided into two doses on the first day of treatment, followed by a maintenance dose of 2.2 mg/kg of body weight (given as a single daily dose or divided into twice daily doses). For pediatric patients weighing over 45 kg, the usual adult dose should be used.

In the treatment of inhalational anthrax (post-exposure) the recommended dose is 2.2 mg/kg of body weight, twice a day in children weighing less than 45 kg. Parenteral therapy is only indicated when oral therapy is not indicated and should not be continued over a prolonged period of time. Oral therapy should be instituted as soon as possible. Therapy must continue for a total of 60 days.

General

The duration of infusion may vary with the dose (100 to 200 mg/day), but is usually one to four hours. A recommended minimum infusion time for 100 mg of a 0.5 mg/mL solution is one hour. Therapy should be continued for at least 24 to 48 hours after symptoms and fever have subsided. The therapeutic antibacterial serum activity will usually persist for 24 hours following recommended dosage.

Intravenous solutions should not be injected intramuscularly or subcutaneously. Caution should be taken to avoid the inadvertent introduction of the intravenous solution into the adjacent soft tissue.

PREPARATION OF SOLUTION

To prepare a solution containing 10 mg/mL, the contents of the vial should be reconstituted with 10 mL (for the 100 mg/vial container) of Sterile Water for Injection or any of the 10 intravenous infusion solutions listed below. Each 100 mg of doxycycline for injection (i.e., withdraw entire solution from the 100 mg vial) is further diluted with 100 mL to 1,000 mL of the intravenous solutions listed below:

1.Sodium Chloride Injection, USP2.5% Dextrose Injection, USP3.Ringer's Injection, USP4.Invert Sugar, 10% in Water5.Lactated Ringer's Injection, USP6.Dextrose 5% in Lactated Ringer's7.Normosol-M® in D5-W8.Normosol-R® in D5-W9.Plasma-Lyte® 56 in 5% Dextrose10.Plasma-Lyte® 148 in 5% Dextrose

This will result in desired concentrations of 0.1 to 1 mg/mL. Concentrations lower than 0.1 mg/mL or higher than 1 mg/mL are not recommended.

Stability

Doxycycline is stable for 48 hours in solution when diluted with Sodium Chloride Injection, USP, or 5% Dextrose Injection, USP, to concentrations between 1 mg/mL and 0.1 mg/mL and stored at 25°C. Doxycycline in these solutions is stable under fluorescent light for 48 hours, but must be protected from direct sunlight during storage and infusion. Reconstituted solutions (1 to 0.1 mg/mL) may be stored up to 72 hours prior to start of infusion if refrigerated and protected from sunlight and artificial light. Infusion must then be completed within 12 hours. Solutions must be used within these time periods or discarded.

Doxycycline, when diluted with Ringer's Injection, USP, or Invert Sugar, 10% in Water, to a concentration between 1 mg/mL and 0.1 mg/mL, must be completely infused within 12 hours after reconstitution to ensure adequate stability. During infusion, the solution must be protected from direct sunlight. Reconstituted solutions (1 to 0.1 mg/mL) may be stored up to 72 hours prior to start of infusion if refrigerated and protected from sunlight and artificial light. Infusion must then be completed within 12 hours. Solutions must be used within these time periods or discarded.

Diluted solutions (0.1 to 1 mg/mL) prepared using Normosol-M® in D5-W; Normosol-R® in D5-W; Plasma-Lyte® 56 in 5% Dextrose; or Plasma-Lyte® 148 in 5% Dextrose may also be stored up to 12 hours prior to start of infusion, if refrigerated and protected from sunlight and artificial light. The infusion must be completed within 12 hours. Solutions must be used within these time periods or discarded.

When diluted with Lactated Ringer's Injection, USP, or Dextrose 5% in Lactated Ringer's, infusion of the solution (ca. 1 mg/mL) or lower concentrations (not less than 0.1 mg/mL) must be completed within six hours after reconstitution to ensure adequate stability. During infusion, the solution must be protected from direct sunlight. Solutions must be used within this time period or discarded.

Solutions of doxycycline for injection, at a concentration of 10 mg/mL in Sterile Water for Injection, when frozen immediately after reconstitution are stable for eight weeks when stored at –20°C. If the product is warmed, care should be taken to avoid heating it after the thawing is complete. Once thawed the solution should not be refrozen.

Parenteral drug products should be inspected visually for particulate matter and discoloration prior to administration, whenever solution and container permit.

HOW SUPPLIED

Doxycycline for Injection, USP, sterile powder, supplied as follows:

Unit of Sale | Strength | Each
NDC 86211-116-10 10 Single-Dose Vials per carton | Doxycycline hyclate equivalent to 100 mg doxycycline per vial | NDC 86211-116-01 20 mL Single-Dose Vial

Store at 20° to 25°C (68° to 77°F) [see USP Controlled Room Temperature].

PROTECT FROM LIGHT

Retain in carton until time of use.

All trademarks are the property of their respective owners.

Distributed by:

Jvet Phannaceuticals, LLC

6925112th Circle North, Suite 101

Largo, FL 33773 USA

Revised date: August 2025

L 116I-VTN R-2508

1313001235-00

PACKAGE LABEL.PRINCIPAL DISPLAY PANEL - CONTAINER LABEL

NDC 86211-116-01 Rx only

Doxycycline for Injection, USP

100 mg per vial

For Intravenous Infusion Only.

MUST BE FURTHER DILUTED

AFTER RECONSTITUTION.

Preservative free. Single-Dose Vial

NDC 86211-116-10 Rx only

Doxycycline for Injection, USP

100 mg per vial

For Intravenous Infusion Only.

MUST BE FURTHER DILUTED AFTER RECONSTITUTION.

Preservative free. 10 x Single-Dose Vials